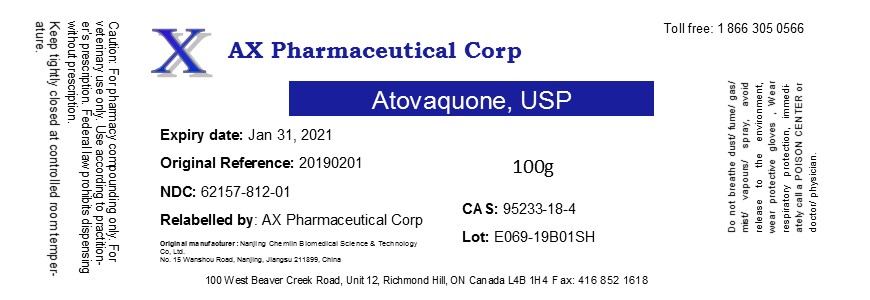 DRUG LABEL: Atovaquone
NDC: 62157-812 | Form: POWDER
Manufacturer: AX Pharmaceutical Corp
Category: other | Type: BULK INGREDIENT
Date: 20190402

ACTIVE INGREDIENTS: ATOVAQUONE 1 g/1 g

Atovaquone